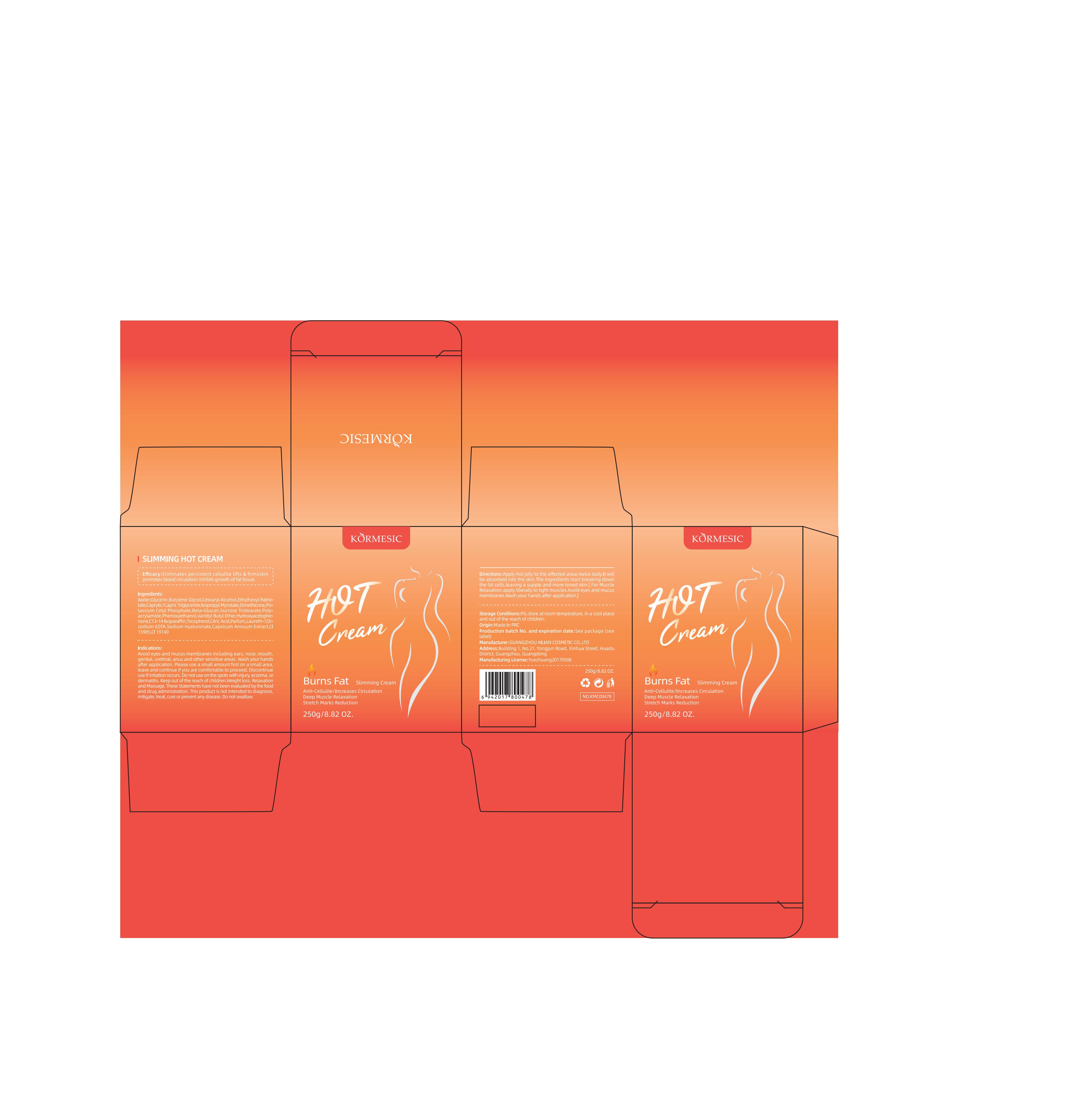 DRUG LABEL: KORMESIC Slimming Hot Cream
NDC: 84372-002 | Form: OINTMENT
Manufacturer: Shenzhen Zhumeng Times Technology Co., Ltd.
Category: otc | Type: HUMAN OTC DRUG LABEL
Date: 20240803

ACTIVE INGREDIENTS: TOCOPHEROL 0.01 g/100 g; GLYCERIN 4 g/100 g
INACTIVE INGREDIENTS: ETHYLHEXYL PALMITATE; PHENOXYETHANOL; EDETATE DISODIUM; FD&C YELLOW NO. 5; POLYACRYLAMIDE (1500 MW); SUCROSE TRISTEARATE; C13-14 ISOPARAFFIN; HYDROXYACETOPHENONE; FD&C YELLOW NO. 6; WATER; CETOSTEARYL ALCOHOL; MEDIUM-CHAIN TRIGLYCERIDES; ISOPROPYL MYRISTATE; CLOMAZONE; LAURETH-7; VANILLYL BUTYL ETHER; CITRIC ACID MONOHYDRATE; POTASSIUM CETYL PHOSPHATE; TRANSFORMING GROWTH FACTOR BETA RECEPTOR TYPE 3; DISPERSE RED 15; HYALURONATE SODIUM; PAPRIKA

Active ingredients

Tocopherol 0.01%
GLYCERIN 4%

Purpose

Eliminates persistent cellulite lifts & firmsskinpromotes blood circulation inhibits growth of fat tissue.

Indications:

Avoid eyes and mucus membranes including ears, nose, mouth,genital, urethral, anus and other sensitive areas. Wash your handsafter application, Please use a small amount first on a small arealeave and continue if you are comfortable to proceed. Discontinueuse if irritation occurs. Do not use on the spots with injury, eczema, ordermatitis. Keep out of the reach of children.Weight loss, Relaxationand Massage, These Statements have not been evaluated by the foodand drug administration. This product is not intended to diagnosemitigate, treat, cure or prevent any disease. Do not swallow.

Warnings

Avoid eyes and mucus membranes including ears, nose, mouth,genital, urethral, anus and other sensitive areas. Wash your handsafter application, Please use a small amount first on a small arealeave and continue if you are comfortable to proceed. Discontinueuse if irritation occurs. Do not use on the spots with injury, eczema, ordermatitis. Keep out of the reach of children.Weight loss, Relaxationand Massage, These Statements have not been evaluated by the foodand drug administration. This product is not intended to diagnosemitigate, treat, cure or prevent any disease. Do not swallow.

Dosage and administration

For external use only.

Do not use

Discontinue use if any irritation or adverse reaction occurs

When using section

Avoid eyes and mucus membranes including ears, nose, mouth,genital, urethral, anus and other sensitive areas. Wash your handsafter application, Please use a small amount first on a small arealeave and continue if you are comfortable to proceed. Discontinueuse if irritation occurs. Do not use on the spots with injury, eczema, ordermatitis. Keep out of the reach of children.Weight loss, Relaxationand Massage, These Statements have not been evaluated by the foodand drug administration. This product is not intended to diagnosemitigate, treat, cure or prevent any disease. Do not swallow.

stop use

Avoid eyes and mucus membranes including ears, nose, mouth,genital, urethral, anus and other sensitive areas. Wash your handsafter application, Please use a small amount first on a small arealeave and continue if you are comfortable to proceed. Discontinueuse if irritation occurs. Do not use on the spots with injury, eczema, ordermatitis. Keep out of the reach of children.Weight loss, Relaxationand Massage, These Statements have not been evaluated by the foodand drug administration. This product is not intended to diagnosemitigate, treat, cure or prevent any disease. Do not swallow.

Keep out of reach of children.

Avoid eyes and mucus membranes including ears, nose, mouth,genital, urethral, anus and other sensitive areas. Wash your handsafter application, Please use a small amount first on a small arealeave and continue if you are comfortable to proceed. Discontinueuse if irritation occurs. Do not use on the spots with injury, eczema, ordermatitis. Keep out of the reach of children.Weight loss, Relaxationand Massage, These Statements have not been evaluated by the foodand drug administration. This product is not intended to diagnosemitigate, treat, cure or prevent any disease. Do not swallow.

Inactive ingredients

WATER

BUTYLENEGLYCOL

CETEARYLALCOHOL

ETHYLHEXYLPALMITATE

CAPRYLIC/CAPRICTRIGLYCERIDE

ISOPROPYLMYRISTATE

DIMETHICONE

POLYACRYLAMIDE

C13-14ISOPARAFFIN

LAURETH-7

SUCROSETRISTEARATE

POTASSIUMCETYLPHOSPHATE

PHENOXYETHANOL

BETA-GLUCAN

VANILLYLBUTYLETHER

HYDROXYACETOPHENONE

CITRICACID

PARFUM

DISODIUMEDTA

SODIUMHYALURONATE

CI15985

CI19140

CAPSICUMANNUUMEXTRACT